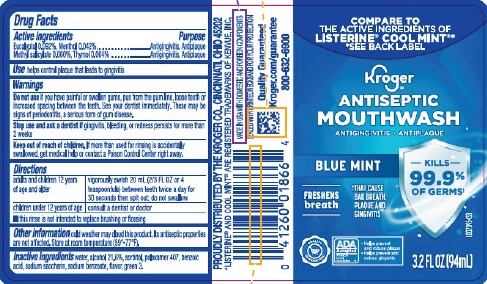 DRUG LABEL: Antispetic
NDC: 30142-664 | Form: MOUTHWASH
Manufacturer: The Kroger Co.
Category: otc | Type: HUMAN OTC DRUG LABEL
Date: 20260227

ACTIVE INGREDIENTS: EUCALYPTOL 0.92 mg/1 mL; MENTHOL 0.42 mg/1 mL; METHYL SALICYLATE 0.6 mg/1 mL; THYMOL 0.64 mg/1 mL
INACTIVE INGREDIENTS: WATER; ALCOHOL; SORBITOL; POLOXAMER 407; BENZOIC ACID; SACCHARIN SODIUM; SODIUM BENZOATE; FD&C GREEN NO. 3

Kroger 664.003/664AT Rev2/AU
Blue Mint Antiseptic Mouthrinse

Active ingredients

Eucalyptol 0.092%

Menthol 0.042%

Methyl salicylate 0.060%

Thymol 0.064%

Purpose

Antigingivitis, Antiplaque

Use

helps control plaque that leads to gingivitis

Warnings

for this product

Do not use

if you have painful or swollen gums, pus from the gum line, loose teeth or increased spacing between the teeth. See your dentist immediately. These may be signs of periodontitis, a serious form of gum disease.

Stop use and ask a dentist if

gingivitis, bleeding, or redness persists for more than 2 weeks.

Keep out of reach of children.

If more than used for rinsing is accidentally swallowed, get medical help or contact a Poison Control Center right away.

Directions

adults and children 12 years of age and older - vigorously swish 20 mL (2/3 FL OZ or 4 teaspoonfuls) between teeth twice a day for 30 seconds then spit out; do not swallow

children under 12 years of age - consult a dentist or doctor

- this rinse is not intended to replace brushing or flossing

Other Information

cold weather may cloud this product. Its antiseptic properties are not affected. Store at room temperature (59⁰ - 77⁰F).

Inactive ingredients

water, alcohol 21.6%, sorbitol, poloxamer 407, benzoic acid, sodium saccharin, sodium benzoate, flavor, green 3

Disclaimer

*LISTERINE® AND COOL MINT® ARE REGISTERED TRADEMARKS OF KENVUE, INC.

Adverse Reactions

PROUDLY DISTRIBUTED BY THE KROGER CO. CINCINNATI, OHIO 45202

MADE IN THE USA WITH DOMESTIC AND FOREIGN COMPONENTS

Quality Guaranteed

Kroger.com/guarantee

800-632-6900

Tamper Evident Statement

SEALED WITH PRINTED NECKBAND FOR YOUR PROTECTION

principal display panel

COMPARE TO THE ACTIVE INGREDIENTS OF LISTERINE® COOL MINT®*

*SEE BACK LABEL

Kroger®

ANTISEPTIC

MOUTHWASH

ANTIGINGIVITIS • ANTIPLAQUE

BLUE MINT

KILLS 99.9% OF GERMS†

FRESHENS breath

†THAT CAUSE BAD BREATH, PLAQUE AND GINGIVITIS

QUALITY GUARANTEED

ADA Accepted

America Dental Association

- Helps prevent and reduce plaque
- Helps prevent and reduce gingivitis

3.2 FL OZ (94 mL)